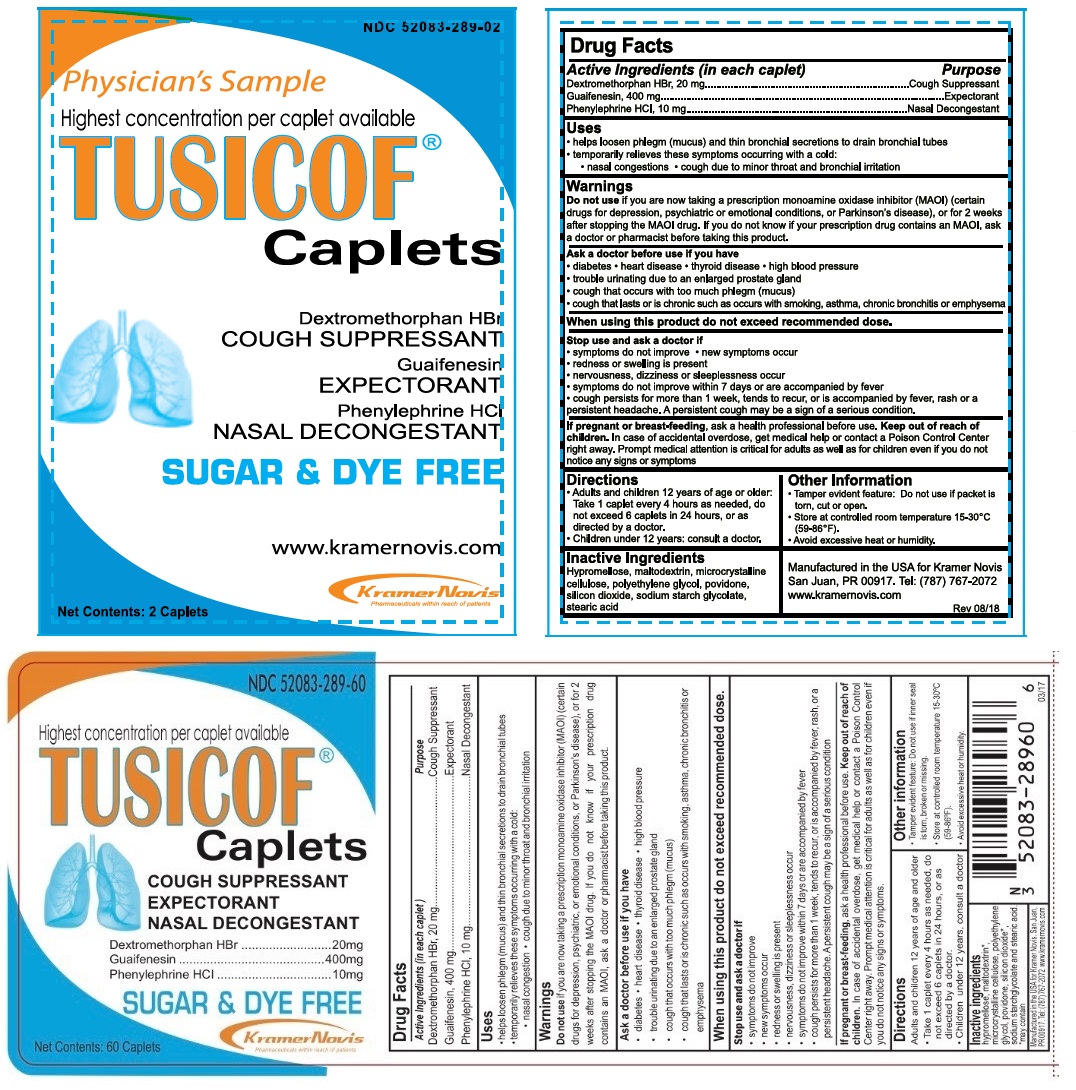 DRUG LABEL: Tusicof
NDC: 52083-289 | Form: TABLET, COATED
Manufacturer: Kramer Novis.
Category: otc | Type: HUMAN OTC DRUG LABEL
Date: 20181215

ACTIVE INGREDIENTS: GUAIFENESIN 400 mg/1 1; DEXTROMETHORPHAN HYDROBROMIDE 20 mg/1 1; PHENYLEPHRINE HYDROCHLORIDE 10 mg/1 1
INACTIVE INGREDIENTS: HYPROMELLOSE, UNSPECIFIED; MALTODEXTRIN; MICROCRYSTALLINE CELLULOSE; POLYETHYLENE GLYCOL, UNSPECIFIED; POVIDONE K30; SILICON DIOXIDE; SODIUM STARCH GLYCOLATE TYPE A POTATO; STEARIC ACID

TUSICOF®

Active Ingredients (in each caplet)

Dextromethorphan HBr, 20 mg

Guaifenesin, 400 mg

Phenylephrine HCl, 10 mg

Purpose

Cough suppressant

Expectorant

Nasal Decongestant

Uses

- helps loosen phlegm (mucus) and thin bronchial secretions to drain bronchial tubes
- temporarily relieves these symptoms occurring with a cold:
  - nasal congestions
  - cough due to minor throat and bronchial irritation

Warnings

Do not use if you are taking a prescription monoamine oxidase inhibitor (MAOI) (certain drugs for depression, psychiatric or emotional conditions, or Parkinson's disease), or for 2 weeks after stopping the MAOI drug. If you do not know if your prescription drug contains an MAOI, ask a doctor or pharmacist before taking this product.

Ask a doctor before use if you have
• diabetes • heart disease • thyroid disease • high blood pressure
• trouble urinating due to an enlarged prostate gland
• cough that occurs with too much phlegm (mucus)
• cough that lasts or is chronic such as occurs with smoking, asthma, chronic bronchitis or emphysema

When using this product do not exceed recommended dose.

Stop use and ask a doctor if
• symptoms do not improve • new symptoms occur
• redness or swelling is present
• nervousness, dizziness or sleeplessness occur
• symptoms do not improve within 7 days or are accompanied by fever
• cough persists for more than 1 week, tends to recur, or is accompanied by fever, rash or a persistent headache. A persistent cough may be a sign of a serious condition.

If pregnant or breast-feeding, ask a health professional before use.

Keep out of reach of children. In case of accidental overdose, get medical help or contact a Poison Control Center right away. Prompt medical attention is critical for adults as well as for children even if you do not notice any signs or symptoms

Directions

Adults and children 12 years of age or older: Take 1 caplet every 4 hours as needed, do not exceed 6 caplets in 24 hours, or as directed by a doctor.

Children under 12 years: consult a doctor.

Other Information

- Tamper evident feature: Do not use if packet is torn, cut or open.
- Store at controlled room temperature 15-30°C (59-86°F).
- Avoid excessive heat and humidity.

Inactive Ingredients

Hypromellose, maltodextrin, microcrystalline cellulose, polyethylene glycol, povidone, silicon dioxide, sodium starch glycolate, stearic acid

Dextromethorphan HBr

COUGH SUPPRESSANT

Guaifenesin

EXPECTORANT

Phenylphrine HCL

NASAL DECONGESTANT

SUGAR & DYE FREE

Manufactured in the USA for Kramer Novis

San Juan, PR 00917. Tel: (787) 767-2072

www.kramernovis.com